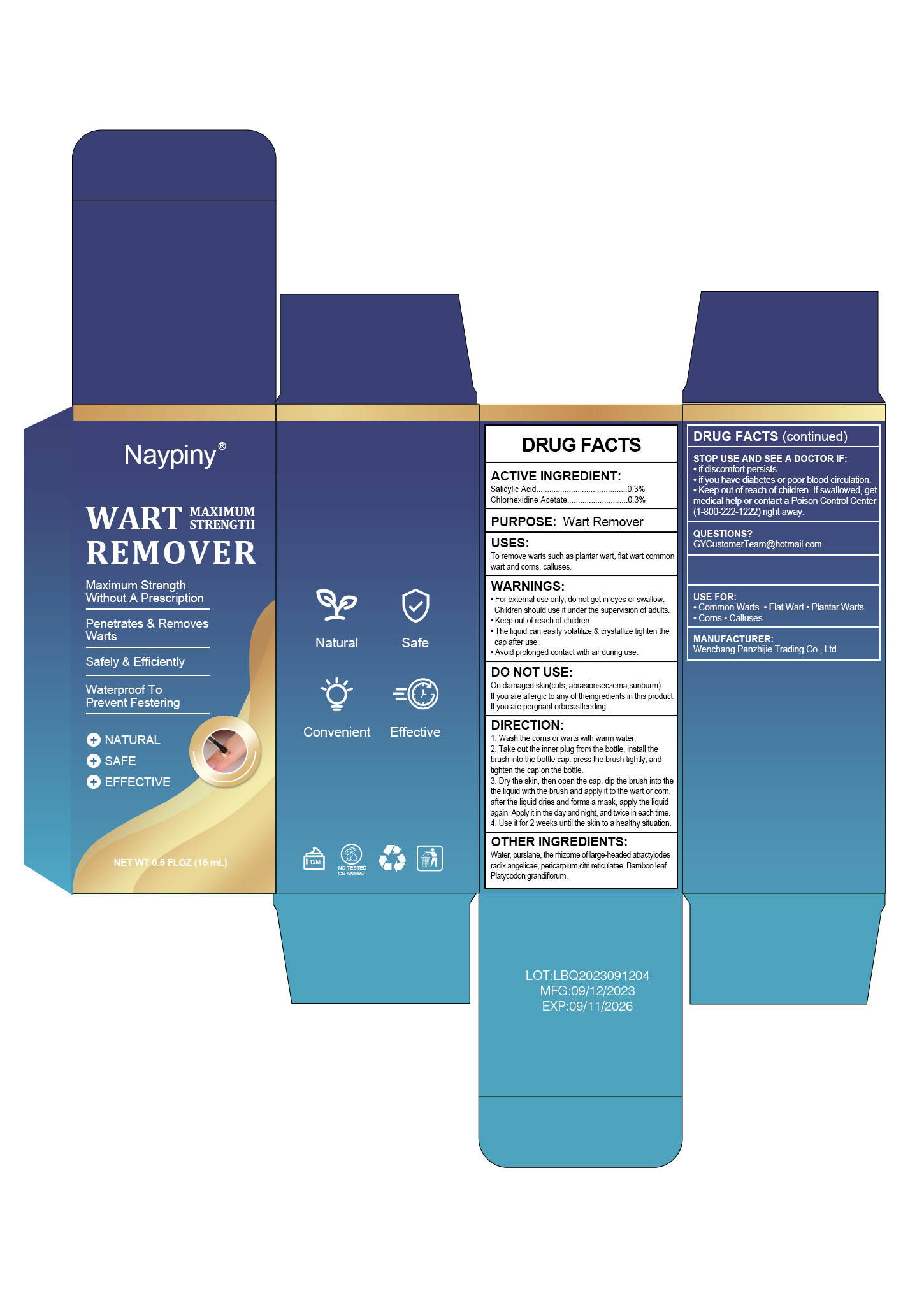 DRUG LABEL: Wart removal
NDC: 83717-002 | Form: LIQUID
Manufacturer: Wenchang Panzhijie Trading Co., Ltd.
Category: otc | Type: HUMAN OTC DRUG LABEL
Date: 20231116

ACTIVE INGREDIENTS: SALICYLIC ACID 0.3 mg/100 mL; CHLORHEXIDINE ACETATE 0.3 mg/100 mL
INACTIVE INGREDIENTS: ANGELICA BISERRATA WHOLE; ATRACTYLODES MACROCEPHALA WHOLE; PURSLANE; PLATYCODON GRANDIFLORUM ROOT; TANGERINE PEEL; WATER; BAMBUSA VULGARIS LEAF

83717-002

ACTIVE INGREDIENT

salicylic acid 0.3%

Chlorhexidine acetate 0.3%

Purpose

wart remover

Use

To remove warts such as plantar wart , flat wart commonwart and coms calluses

Warnings

For extemal use only , do not get in eyes or swallow. Children should use it under the supervision of adults.

Keep out of reach of children

The liquid can easily volatilize & crystallize tighten thecap after use

Avoid prolonged contact with air during use

Do not use

On damaged skin (cuts , abrasionseczema , sunburn)

If you are allergic to any of the ingredients in this product .

If you are pregnant or breastfeeding

STOP USE AND SEE A DOCTOR IF

if discomfort persists

if you have diabetes or poor blood circulation

Keep out of reach of children . If swallowed , get medical help or contact a Poison Control Center(1-800-222-1222) nght away .

Keep out of reach of children . If swallowed , get medical help or contact a Poison Control Center(1-800-222-1222) nght away .

Directions

1 . Wash the coms or warts with wam water

2 . Take out the inner plug from the bottle , install thebrush into the bottle cap . press the brush tightly , and tighten the cap on the bottle

3 . Dry the skin , then open the cap , dip the brush into thethe liquid with the brush and apply it to the wart or com .after the liquid dnes and forms a mask , apply the liquid again Apply t in the day and night , and twice in each time

4 . Use t for 2 weeks untl the skin to a healthy situation

Inactive ingredients

water, purslane , the rhizome of large-headed atractylodes, radix angelicae , pericarpium citri reticulata, Bamboo leaf , Platycodon grandiflorum